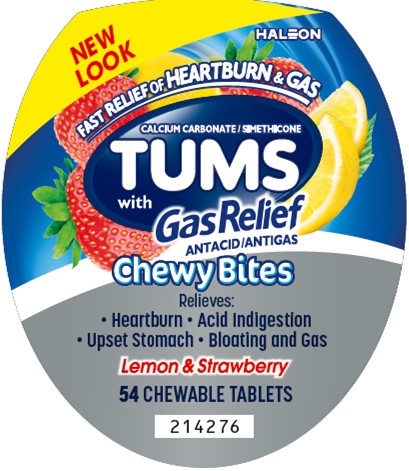 DRUG LABEL: Tums Chewy Bites with Gas Relief
NDC: 0135-0624 | Form: TABLET, CHEWABLE
Manufacturer: Haleon US Holdings LLC
Category: otc | Type: HUMAN OTC DRUG LABEL
Date: 20250708

ACTIVE INGREDIENTS: CALCIUM CARBONATE 750 mg/1 1; DIMETHICONE, UNSPECIFIED 80 mg/1 1
INACTIVE INGREDIENTS: ALCOHOL; AMMONIA; YELLOW WAX; CARNAUBA WAX; CITRIC ACID MONOHYDRATE; COCONUT OIL; STARCH, CORN; CORN SYRUP; ICODEXTRIN; ETHYL ACETATE; FD&C BLUE NO. 1 ALUMINUM LAKE; FD&C RED NO. 40; ALUMINUM OXIDE; FD&C YELLOW NO. 5 ALUMINUM LAKE; FD&C YELLOW NO. 6; ACACIA; ISOPROPYL ALCOHOL; MALTODEXTRIN; MEDIUM-CHAIN TRIGLYCERIDES; METHYLPARABEN; MODIFIED CORN STARCH (1-OCTENYL SUCCINIC ANHYDRIDE); BUTYL ALCOHOL; PHOSPHORIC ACID; PROPYLENE GLYCOL; PROPYLPARABEN; WATER; SHELLAC; SODIUM BENZOATE; SORBIC ACID; SORBITOL; SOYBEAN OIL; SOYBEAN LECITHIN; SUCROSE; TERT-BUTYLHYDROQUINONE; TITANIUM DIOXIDE; CORN OIL

Drug Facts

Active ingredients (per tablet)

Calcium carbonate USP 750 mg

Simethicone USP 80 mg

Purposes

Antacid

Antigas

Uses

relieves

- heartburn
- acid indigestion
- sour stomach
- upset stomach associated with these symptoms
- gas associated with heartburn, sour stomach, or acid indigestion

Warnings

Ask a doctor or pharmacist before use if you are

presently taking a prescription drug. Antacids may interact with certain prescription drugs.

When using this product

- do not take more than 6 tablets in 24 hours
- if pregnant do not take more than 6 tablets in 24 hours
- do not use the maximum dosage for more than 2 weeks, except under the advice and supervision of a doctor

Directions

- adults and children 12 years of age and over: chew 1-2 tablets as symptoms occur, or as directed by a doctor. Chew or crush tablets completely before swallowing.
- do not take for symptoms that persist for more than 2 weeks unless advised by a doctor

Other information

- each chewable tablet contains: elemental calcium 300 mg
- do not store above 25°C (77°F)
- contains FD&C Yellow No.5 (tartrazine) as a color additive

Inactive ingredients

alcohol, ammonium hydroxide, beeswax, carnauba wax, citric acid, coconut oil, corn starch, corn syrup, dextrin, ethyl acetate, ethyl alcohol, FD&C blue #1 alum lake, FD&C red #40, FD&C red #40 alum lake, FD&C yellow #5 alum lake (tartrazine), FD&C yellow #6 alum lake, flavors, gum arabic, isopropyl alcohol, maltodextrin, medium-chain triglycerides, methylparaben, modified corn starch, n-butyl alcohol, phosphoric acid, propylene glycol, propylparaben, purified water, shellac, sodium benzoate, sorbic acid, sorbitol, soy bean oil, soy lecithin, sucrose, tert-butylhydroquinone, titanium dioxide, vegetable oil

Questions or comments?

Call toll-free 1-800-897-7535

Additional Information

Safety sealed – Do not use if printed inner seal beneath cap is missing or broken.

Principal Display Panel

NEW LOOK

HALEON

FAST RELIEF OF HEARTBURN & GAS

CALCIUM CARBONATE / SIMETHICONE

TUMS with Gas Relief

ANTACID/ANTIGAS

Chewy Bites

Relieves:

- Heartburn
- Acid Indigestion
- Upset Stomach
- Bloating and Gas

Lemon & Strawberry

54 CHEWABLE TABLETS